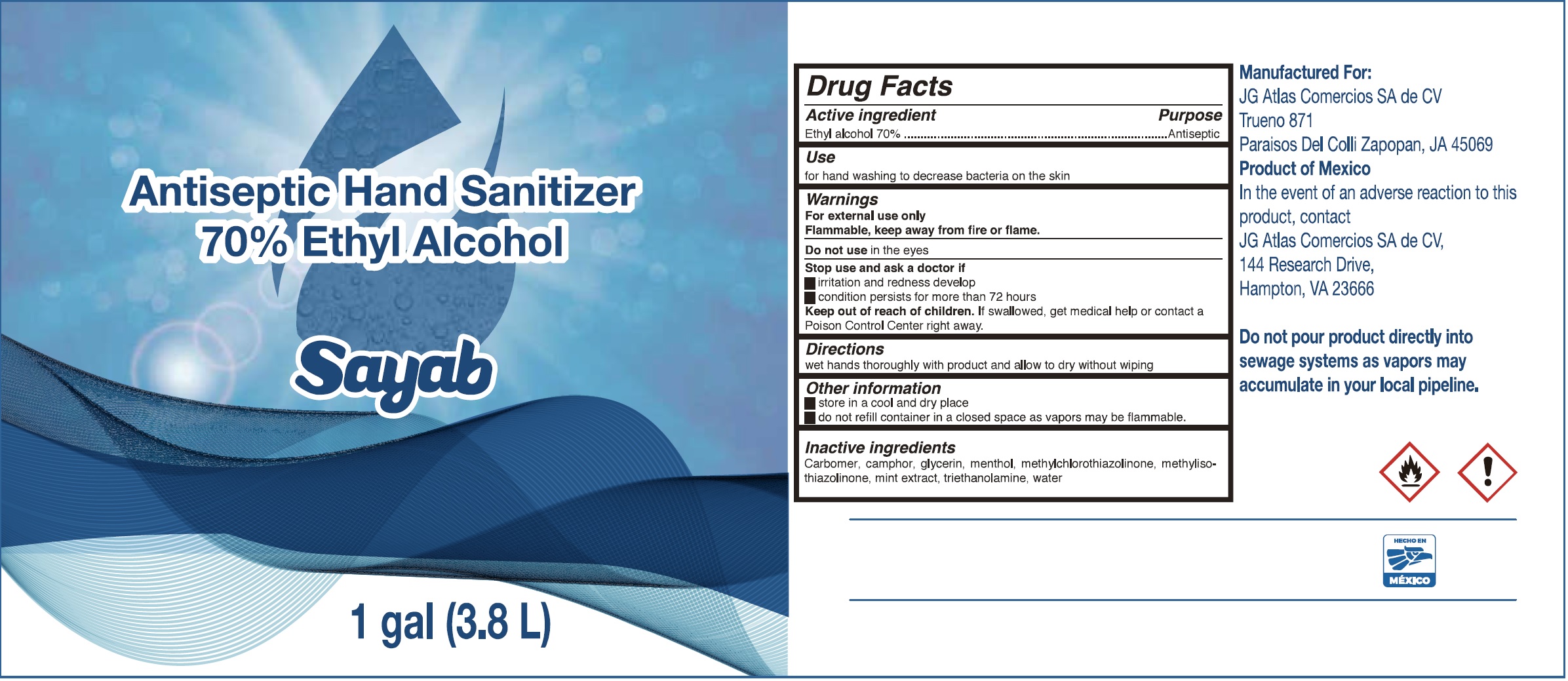 DRUG LABEL: Antisepctic Hand Sanitizer 100
NDC: 75292-001 | Form: GEL
Manufacturer: JG Atlas Comercios, S.A. de C.V.
Category: otc | Type: HUMAN OTC DRUG LABEL
Date: 20200428

ACTIVE INGREDIENTS: ALCOHOL 0.75 mL/1 mL
INACTIVE INGREDIENTS: CAMPHOR (SYNTHETIC); CARBOMER HOMOPOLYMER, UNSPECIFIED TYPE; MENTHOL; METHYLCHLOROISOTHIAZOLINONE; METHYLISOTHIAZOLINONE; TROLAMINE; WATER

Antisepctic Hand Sanitizer 100% Ethyl Alcohol

Active Ingredient

Ethyl alcohol 70%

Purpose

Antiseptic

Use

for hand washing to decrease bacteria on the skin

Warnings

For external use only.
Flammable, keep away from fire or flame.

Do not use

in the eyes

Stop using and ask a doctor if

- irritation and redness develop
- condition persists for more than 72 hours

Keep out of reach of children

If swallowed, get medical help or contact a Poison Control Center right away.

Directions

wet hands thoroughly with product and allow to dry without wiping

Other information

- store in a cool and dry place
- do not refill container in a closed space as vapors may be flammable.

Inactive ingredients

camphor, carbomer, glycerin, menthol, methylchlorothiazolinone, methylisothiazolinone, mint extract, triethanolamine, water